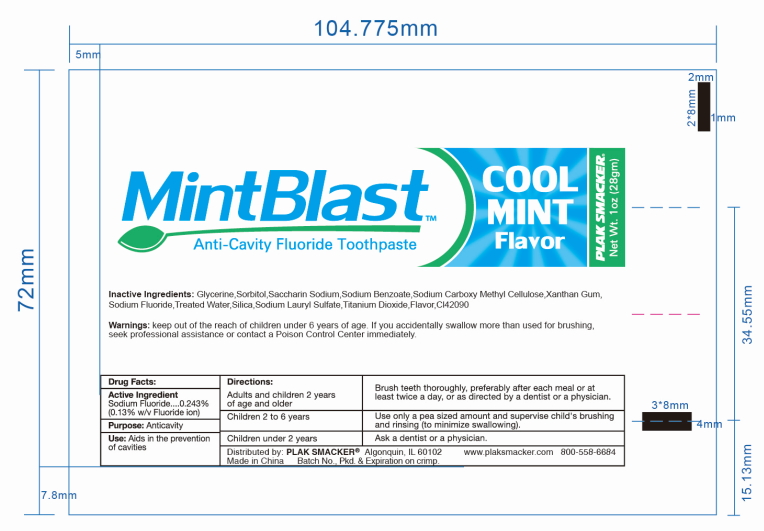 DRUG LABEL: MINTBLAST
NDC: 72326-8011 | Form: PASTE
Manufacturer: YOUNG PS ACQUISITION, LLC
Category: otc | Type: HUMAN OTC DRUG LABEL
Date: 20180528

ACTIVE INGREDIENTS: SODIUM FLUORIDE 2.43 mg/1 g
INACTIVE INGREDIENTS: SORBITOL; SILICON DIOXIDE; WATER; GLYCERIN; SODIUM LAURYL SULFATE; TITANIUM DIOXIDE; CARBOXYMETHYLCELLULOSE SODIUM; SACCHARIN SODIUM; SODIUM BENZOATE; XANTHAN GUM

MINTBLAST ANTICAVITY FLUORIDE TOOTH PASTE

Active ingredient

Sodium Fluoride - 0.243% (0.13% w/v Fluoride ion)

Purpose

Anticavity

Use

Aids in the prevention of cavities.

Directions :

- Adults and children 2 years of age and older: Brush teeth thoroughly, preferably after each meal or at least twice a day, or use as directed by a dentist or a physician.
- Children 2 to 6 years: Use only a pea sized amount and supervise child's brushing and rinsing (to minimize swallowing) .
- Children under 2 year : Ask a dentist or physician .

Warnings

Keep out of the reach of children under 6 years of age. If you accidentally swallow more than used for brushing, seek professional assistance or contact a Poison Control Center immediately.

Inactive Ingredients

Glycerine, Sorbitol, Saccharin Sodium, Sodium Benzoate, Sodium Carboxy Methyl Cellulose, Xanthan Gum, Treated Water, Silica, Sodium Lauryl Sulfate, Titanium Dioxide, Flavor, CI42090